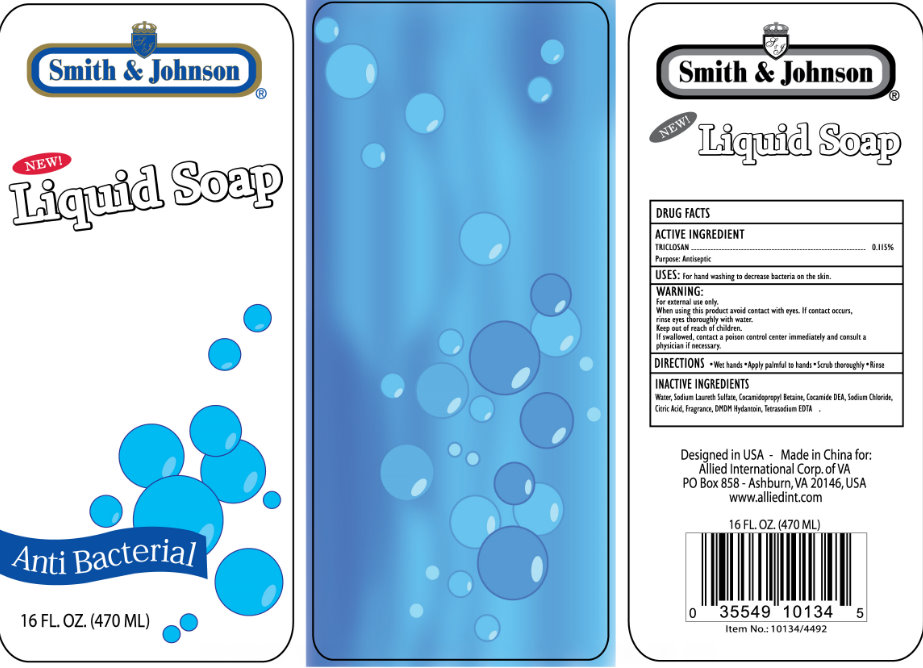 DRUG LABEL: Smith and Johnson Antibacterial
NDC: 52546-100 | Form: LIQUID
Manufacturer: Allied International Corp
Category: otc | Type: HUMAN OTC DRUG LABEL
Date: 20160928

ACTIVE INGREDIENTS: TRICLOSAN 115 mg/100 mL
INACTIVE INGREDIENTS: CITRIC ACID MONOHYDRATE; SODIUM CHLORIDE; EDETATE SODIUM; WATER; DMDM HYDANTOIN; SODIUM LAURETH SULFATE; COCAMIDOPROPYL BETAINE; COCO DIETHANOLAMIDE

Smith and Johnson Antibacterial Liquid Soap

Active ingredient

Triclosan 0.115 percent

Uses

For handwashing to decrease bacteria on the skin.

Warnings

For external use only.

When using this product avoid contact with eyes. If contact occurs, rinse eyes thoroughly with water.

Keep out of reach of children.

If swallowed, contact a poison control center immediately and consult a physician if necessary.

Directions

Wet hands. Apply palmful to hands. Scrub thoroughly . Rinse

Inactive Ingredients

Water, Sodium Laureth Sulfate, Cocamidopropyl Betaine, Cocamide DEA, Sodium Chloride, Citric Acid, Fragrance, DMDM Hydantoin, Tetrasodium EDTA

DESCRIPTION

Designed in USA

Made in China for

Allied International Corp of VA

PO Box 858 Ashburn, VA 20146 USA

www.alliedint.com

Keep out of reach of children.

If swallowed, contact a poison control center immediately and consult a physician if necessary.

Purpose:

Antiseptic

PACKAGE LABEL

Smith and Johnson

New

Liquid Soap

Antibacterial

16 FL OZ (470 ML)